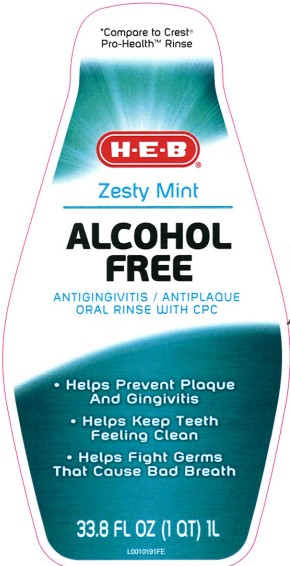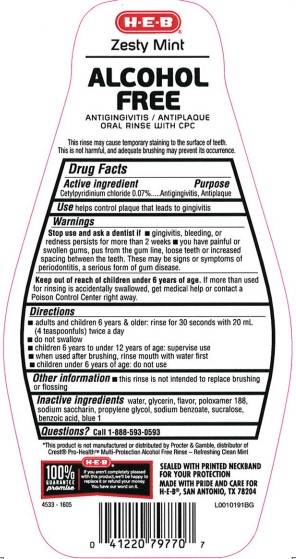 DRUG LABEL: Alcohol Free
NDC: 37808-299 | Form: MOUTHWASH
Manufacturer: H E B
Category: otc | Type: HUMAN OTC DRUG LABEL
Date: 20260224

ACTIVE INGREDIENTS: CETYLPYRIDINIUM CHLORIDE 0.7 mg/1 mL
INACTIVE INGREDIENTS: WATER; GLYCERIN; POLOXAMER 188; SACCHARIN SODIUM; PROPYLENE GLYCOL; SODIUM BENZOATE; SUCRALOSE; BENZOIC ACID; FD&C BLUE NO. 1

HEB 299.005/299AK-AL
Multi Action Alcohol Free Antiseptic Rinse w/CPC

Claims

HEB®

Zesty Mint

ALCOHOL FREE

ANTIGINGIVITIS/ANTIPLAQUE ORAL RINSE WITH CPC

This rinse may cause temporary staining to the surface of teeth.

This is not harmful, and adequate brushing may prevent its occurrence.

Active ingredient

Cetylpyridinium chloride 0.07%

Purpose

Antigingivitis, Antiplaque

Use

helps control plaque that leads to gingivitis

Warnings

for this product

Stop use and ask a dentist

- gingivitis, bleeding, or redness persists for more than 2 weeks
- you have painful or swollen gums, pus from the gum line, loose teeth or increased spacing bwtween the teeth. These may be signs or symptoms of periodontitis, a serious form of gum disease.

Keep out of reach of children under 6 years of age

If more than used for rinsing is accidentally swallowed, get medical help or contact a poison Control Center right away.

Directions

- adults and children 6 years & older: rinse for 30 seconds with 20 mL (4 teaspoonfuls) twice a day
- do not swallow
- children 6 years to under 12 years of age: supervise use
- when used after brushing, rinse mouth with water first
- children under 6 years of age: do not use

Other information

- this rinse is not intended to replace brushing of flossing

Inactive ingredients

water, glycerin, flavor, poloxamer 188, sodium saccharin, propylene glycol, sodium benzoate, sucralose, benzoic acid, blue 1

Questions?

Call 1-888-593-0593

Disclaimer

*This product is not manufactured or distributed by Procter & Gamble, distributor of Crest®Pro-Health Multi-Protection Alcohol Free Rinse - Refreshing Clean Mint.

SEALED WITH PRINTED NECKBAND FOR YOUR PROTECTION

MADE WITH PRIDE AND CARE FOR H-E-B®, SAN ANTONIO, TX 78204

HEB100% GUARANTEE promise

If you aren't completely pleased with this product, we'll be happy to replace it or refund your money. You have our word on it.

principal display panel

*Compare to Crest®Pro-Health™ Rinse

H-E-B®

Zesty Mint

ALCOHOL FREE

ANTIGINGIVITIS/ANTIPLAQUE

ORAL RINSE WITH CPC

- Helps Prevent Plaque And Gingivitis
- Helps Keep Teeth Feeling Clean
- Helps Fight Germs That Cause Bad Breath

33.8 FL OZ (1 QT) 1 L